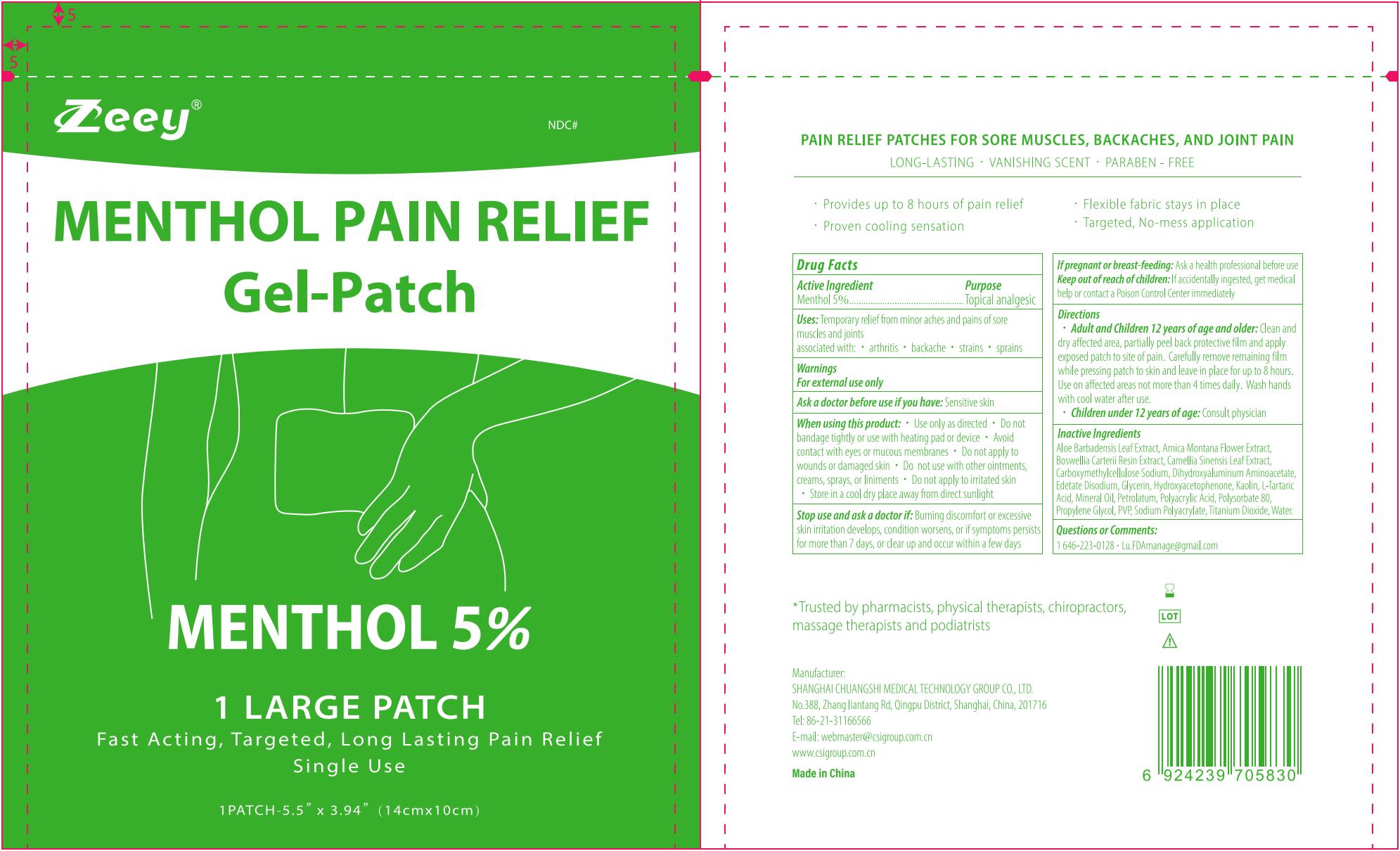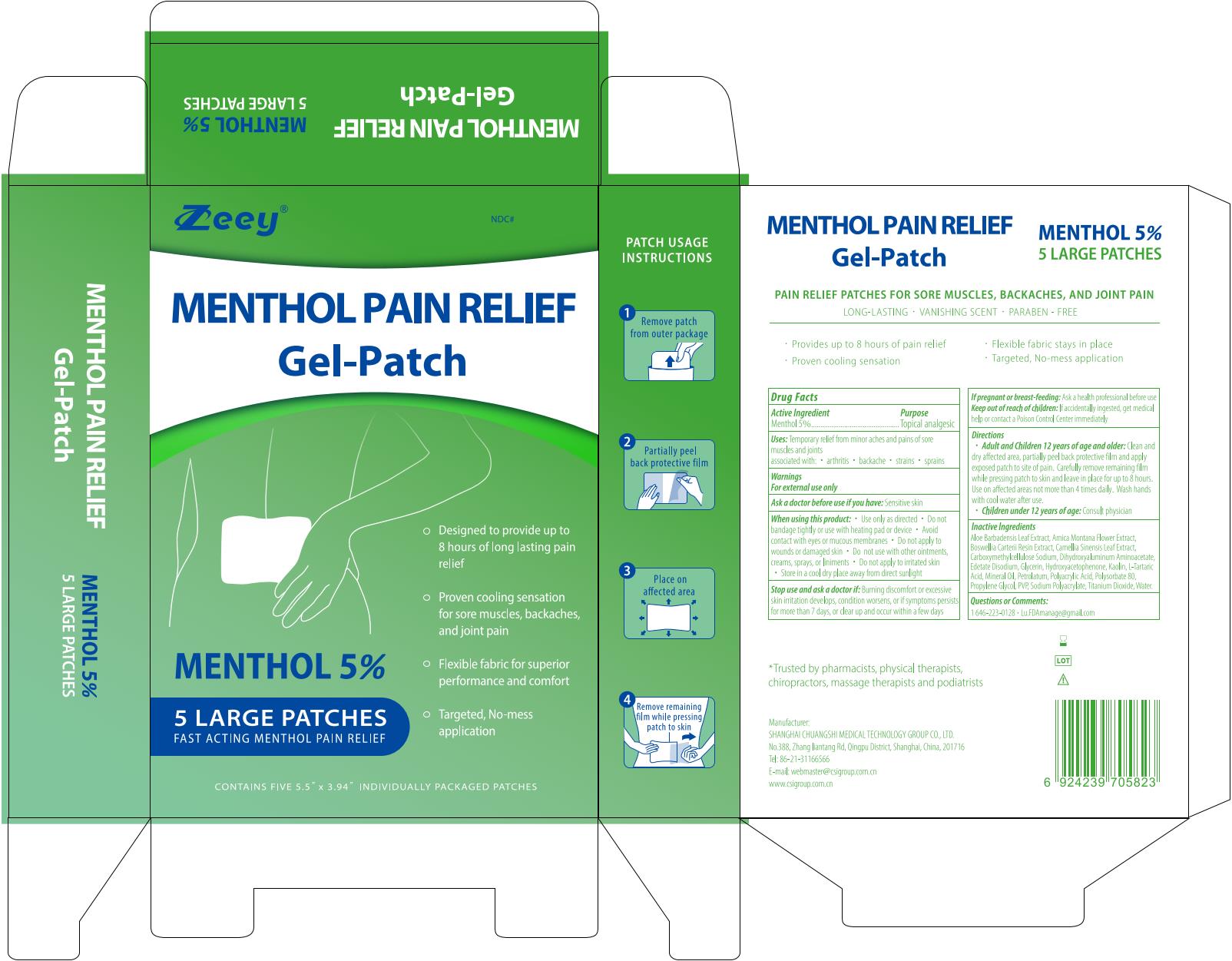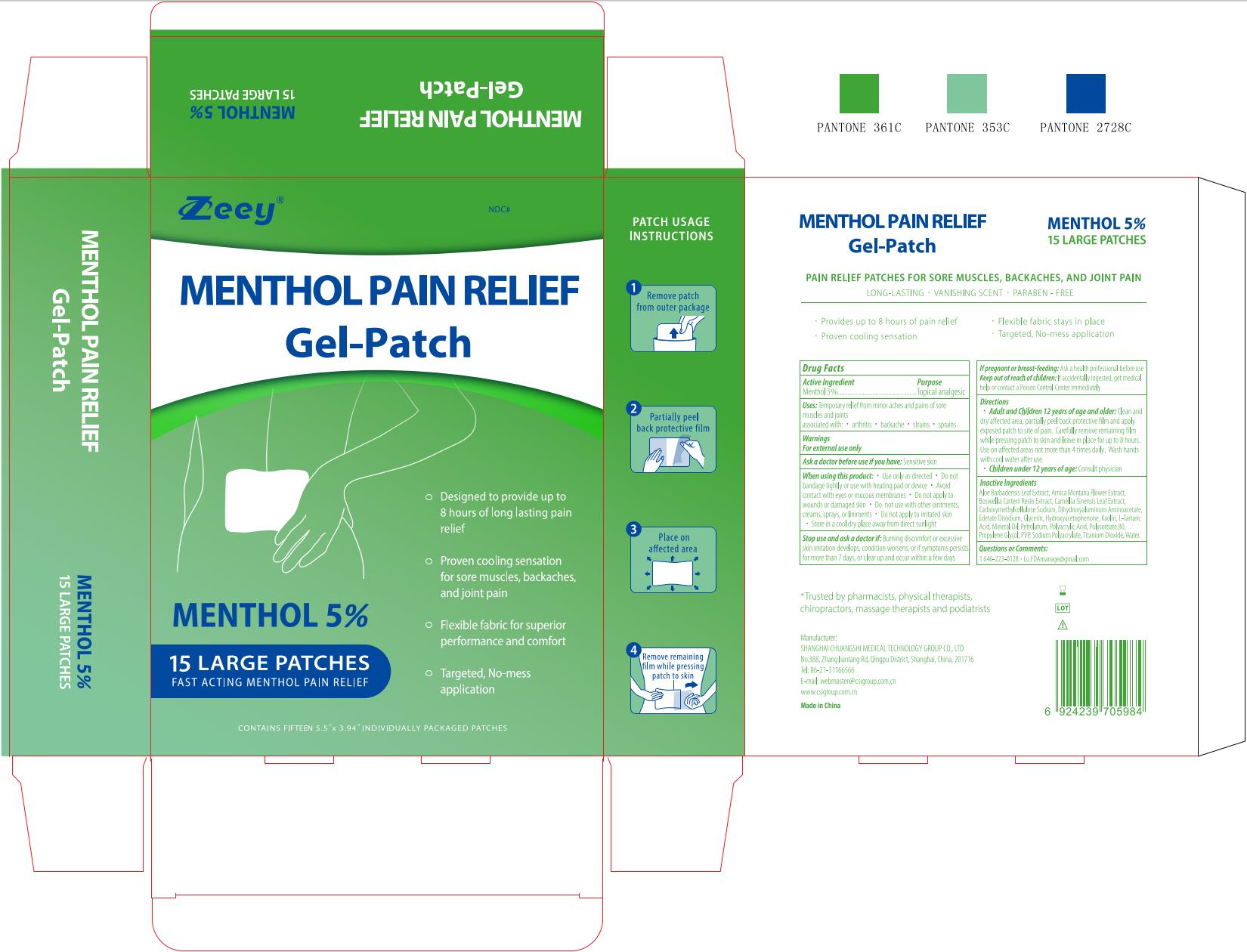 DRUG LABEL: MENTHOL PAIN RELIEF Gel-Patch
NDC: 73557-131 | Form: PATCH
Manufacturer: Shanghai Chuangshi Medical Technology (Group) Co., Ltd.
Category: otc | Type: HUMAN OTC DRUG LABEL
Date: 20240429

ACTIVE INGREDIENTS: MENTHOL 0.05 g/1 g
INACTIVE INGREDIENTS: ARNICA MONTANA FLOWER; FRANKINCENSE; KAOLIN; TARTARIC ACID; WATER; DIHYDROXYALUMINUM AMINOACETATE ANHYDROUS; PROPYLENE GLYCOL; POLYACRYLIC ACID (250000 MW); CARBOXYMETHYLCELLULOSE SODIUM; SODIUM POLYACRYLATE (2500000 MW); TITANIUM DIOXIDE; MINERAL OIL; PETROLATUM; HYDROXYACETOPHENONE; POLYSORBATE 80; GLYCERIN; POVIDONE K90; GREEN TEA LEAF; ALOE VERA LEAF; EDETATE DISODIUM

Zeey MENTHOL PAIN RELIEF Gel-Patch, 5 & 15 Patches

Active Ingredient

Menthol 5.0%

Purpose

Topical Analgesic

Uses:

Temporary relief from minor aches and pains of sore muscles and joints

associated with: ·arthrits ·backache ·strains ·sprains

Warnings

For external use only

Ask a doctor before use if you have:

Sensitive skin

When using this product:

·Use only as directed ·Do not bandage tightly or use with heating pad or device ·Avoid contact with eyes or mucous membranes ·Do not apply to wounds or damaged skin ·Do not use with other ointments, creams, sprays, or liniments ·Do not apply to irritated skin ·Store in a cool dry place away from direct sunlight

Stop use and ask a doctor if:

Burning disconfort or excessive skin irritation develops, condition worsens, or if symptoms persist for more than 7 days, or clear up and occur again within a few days

If pregnant or breast-feeding:

Ask a health professional before use

Keep out of reach of children:

If accidentally ingested, get medical help or contact a Poison Control Center immediately

Directions

· Adult and Children 12 years of age and older:Clean and dry affected area, partially peel back protective film and apply exposed patch to site of pain. Carefully remove remaining film while pressing patch to skin and leave in place for up to 8 hours. Use on affected areas not more than 4 times daily. Wash hands with cool water after use.

· Children under 12 years of age: Consult physician

Inactive Ingredients

Aloe Barbadensis Leaf Extract, Arnica Montana Flower Extract, Boswellia Carterii Resin Extract, Camellia Sinensis Leaf Extract, Carboxymethylcellulose Sodium, Dihydroxyaluminum Aminoacetate, Edetate Disodium, Glycerin, Hydroxyacetophenone, Kaolin, L-Tartaric Acid, Mineral Oil, Petrolatum, Polyacrylic Acid, Polysorbate 80, Propylene Glycol, PVP, Sodium Polyacrylate, Titanium dioxide, Water

Questions or Comments:

1 646-223-0128 ·Lu.FDAmanage@gmail.com

STORAGE AND HANDLING

·Store in a cool dry place away from direct sunlight